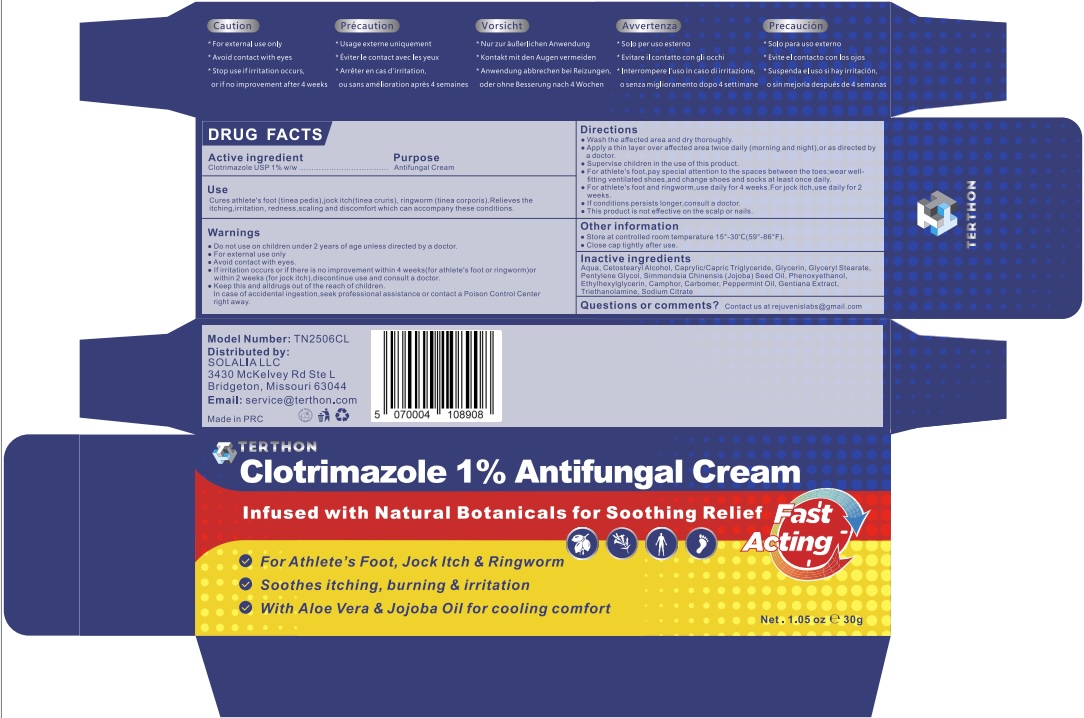 DRUG LABEL: Terthon Clotrimazole 1% Antifungal Cream
NDC: 85849-010 | Form: CREAM
Manufacturer: SOLALIA LLC
Category: otc | Type: HUMAN OTC DRUG LABEL
Date: 20251222

ACTIVE INGREDIENTS: CLOTRIMAZOLE 1 g/100 g
INACTIVE INGREDIENTS: PEPPERMINT OIL; SIMMONDSIA CHINENSIS (JOJOBA) SEED OIL; PHENOXYETHANOL; CAMPHOR (SYNTHETIC); SODIUM CITRATE; CARBOMER; AQUA; GLYCERYL STEARATE; CETOSTEARYL ALCOHOL; PENTYLENE GLYCOL; TRIETHANOLAMINE; GENTIANA SCABRA ROOT; CAPRYLIC/CAPRIC TRIGLYCERIDE; GLYCERIN; ETHYLHEXYLGLYCERIN

Initial Drug Listing - Terthon Clotrimazole 1% Antifungal Cream

ACTIVE INGREDIENT

Clotrimazole 1%

PURPOSE

Antifungal

INDICATIONS AND USAGE

Cures athlete's foot (tinea pedis), jock itch (tinea cruris), ringworm (tinea corporis). Relieves the itching, irritation, redness, scaling and discomfort which can accompany these conditions.

WARNINGS

For external use only

WHEN USING

Avoid contact with eyes.

DO NOT USE

on children under 2 years of age unless directed by a doctor.

STOP USE

If irritation occurs or if there is no improvement within 4 weeks (for athlete's foot or ringworm) or within 2 weeks (for jock itch), discontinue use and consult a doctor.

KEEP OUT OF REACH OF CHILDREN

Keep out of the reach of children. In case of accidental ingestion, seek professional assistance or contact a Poison Control Center right away.

DOSAGE AND ADMINISTRATION

• Wash the affected area and dry thoroughly.
• Apply a thin layer over affected area twice daily (morning and night), or as directed by a doctor.
• Supervise children in the use of this product.
• For athlete's foot, pay special attention to the spaces between the toes; wear well-fitting ventilated shoes, and change shoes and socks at least once daily.
• For athlete's foot and ringworm, use daily for 4 weeks. For jock itch, use daily for 2 weeks.
• If conditions persists longer, consult a doctor.
• This product is not effective on the scalp or nails.

OTHER SAFETY INFORMATION

• Store at controlled room temperature 15°–30°C (59°–86°F).
• Close cap tightly after use.

INACTIVE INGREDIENT

Aqua, Cetostearyl Alcohol, Caprylic/Capric Triglyceride, Glycerin, Glyceryl Stearate, Pentylene Glycol, Simmondsia Chinensis (Jojoba) Seed Oil, Phenoxyethanol, Ethylhexylglycerin, Camphor, Carbomer, Peppermint Oil, Gentiana Extract, Triethanolamine, Sodium Citrate

QUESTIONS

Contact us at rejuvenislabs@gmail.com